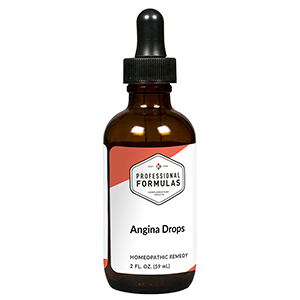 DRUG LABEL: Angina Drops
NDC: 63083-2083 | Form: LIQUID
Manufacturer: Professional Complementary Health Formulas
Category: homeopathic | Type: HUMAN OTC DRUG LABEL
Date: 20190815

ACTIVE INGREDIENTS: HAWTHORN LEAF WITH FLOWER 2 [hp_X]/59 mL; SELENICEREUS GRANDIFLORUS STEM 3 [hp_X]/59 mL; KALMIA LATIFOLIA LEAF 3 [hp_X]/59 mL; PHOSPHORUS 5 [hp_X]/59 mL; ARSENIC TRIOXIDE 6 [hp_X]/59 mL; DIGITALIS 6 [hp_X]/59 mL; NITROGLYCERIN 6 [hp_X]/59 mL; DRIMIA MARITIMA BULB 6 [hp_X]/59 mL; GELSEMIUM SEMPERVIRENS ROOT 6 [hp_X]/59 mL; SPIGELIA MARILANDICA ROOT 6 [hp_X]/59 mL; POTASSIUM CARBONATE 12 [hp_X]/59 mL; ARNICA MONTANA WHOLE 30 [hp_X]/59 mL
INACTIVE INGREDIENTS: ALCOHOL; WATER

C83

ACTIVE INGREDIENTS

Crataegus oxyacantha 2X
Cactus grandiflorus 3X
Kalmia latifolia 3X
Phosphorus 5X
Arsenicum album 6X
Digitalis purpurea 6X
Glonoinum 6X
Scilla maritima 6X
Gelsemium sempervirens 6X, 12X
Spigelia marilandica 6X, 12X
Kali carbonicum 12X, 30X
Arnica montana 30X

QUESTIONS

Professional Formulas

PO Box 2034 Lake Oswego, OR 97035

INDICATIONS

For the temporary relief of muscle cramps or spasms, muscular debility, mild abdominal, back or chest pain, or anxiousness.*

PURPOSE

*Claims based on traditional homeopathic practice, not accepted medical evidence. Not FDA evaluated.

WARNINGS

Seek medical attention immediately for severe symptoms such as chest pressure or tightness with radiation of the pain to the jaw and down the arm, shortness of breath, or sweating. Keep out of the reach of children. In case of overdose, get medical help or contact a poison control center right away. If pregnant or breastfeeding, ask a healthcare professional before use.

Keep out of the reach of children.

PREGNANCY OR BREAST FEEDING

If pregnant or breastfeeding, ask a healthcare professional before use.

DIRECTIONS

Place drops under tongue 30 minutes before/after meals. Adults and children 12 years and over: Take 10 drops up to 3 times per day. Consult a physician for use in children under 12 years of age.

OTHER INFORMATION

Tamper resistant. If seal is broken, do not use. After opening, close container tightly and store at room temperature away from heat.

INACTIVE INGREDIENTS

20% ethanol, purified water.

LABEL

Est 1985

Professional Formulas

Complementary Health

Angina Drops

Homeopathic Remedy

2 FL. OZ. (59 mL)